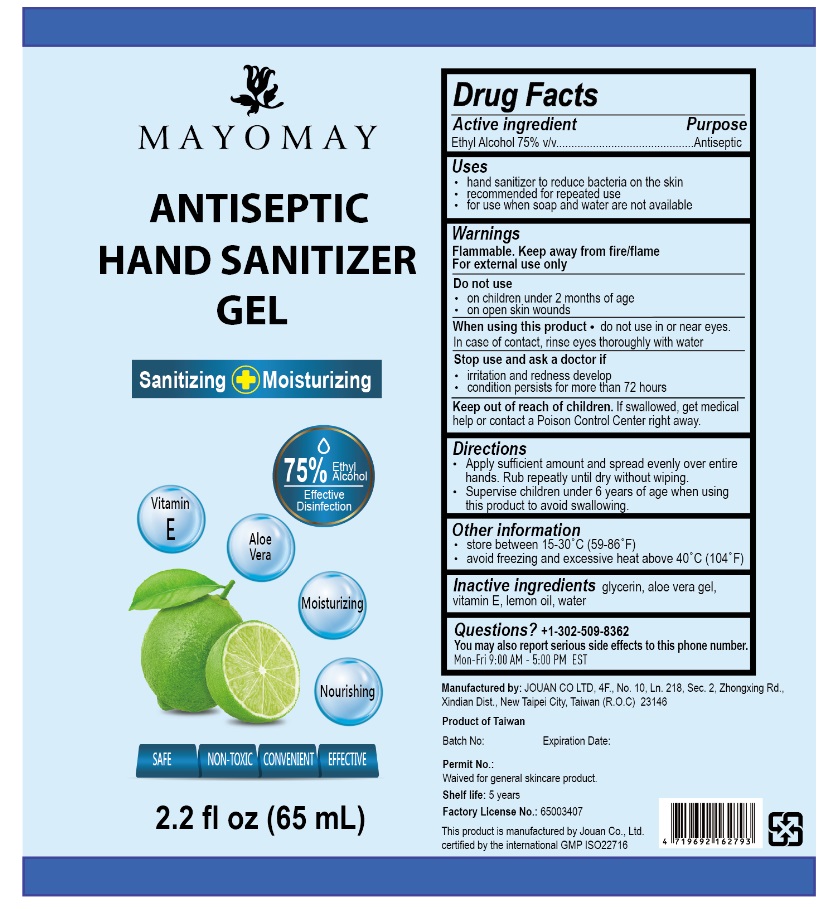 DRUG LABEL: ANTISEPTIC HAND SANITIZER
NDC: 79302-302 | Form: GEL
Manufacturer: JOUAN CO., LTD.
Category: otc | Type: HUMAN OTC DRUG LABEL
Date: 20200701

ACTIVE INGREDIENTS: ALCOHOL 75 mL/100 mL
INACTIVE INGREDIENTS: GLYCERIN; ALOE VERA LEAF; .ALPHA.-TOCOPHEROL; LEMON OIL; WATER

MAYOMAY ANTISEPTIC HAND SANITIZER GEL

Active ingredient

Ethyl Alcohol 75% v/v

Purpose

Antiseptic

Uses

- hand sanitizer to reduce bacteria on the skin
- recommended for repeated use
- for use when soap and water are not available

Warnings

Flammable. Keep away from fire/flame

For external use only

Do not use

- on children under 2 months of age
- on open skin wounds

When using this product • do not use in or near eyes. In case of contact, rinse eyes thoroughly with water

Stop use and ask a doctor if

- irritation and redness develop
- condition persists for more than 72 hours

Keep out of reach of children. If swallowed, get medical help or contact a Poison Control Center right away.

Directions

- Apply sufficient amount and spread evenly over entire hands. Rub repeatly until dry without wiping.
- Supervise children under 6 years of age when using this product to avoid swallowing.

Other information

- store between 15-30°C (59-86° F)
- avoid freezing and excessive heat above 40°C (104°F)

Inactive ingredients

glycerin, aloe vera gel, vitamin E, lemon oil, water

Questions?

+1-302-509-8362

You may also report serious side effects to this phone number.

Mon-Fri 9:00 AM - 5:00 PM EST

Sanitizing Moisturizing

Effective Disinfection

Vitamin E, Aloe Vera, Moisturizing, Nourishing

SAFE, NON-TOXIC, CONVENIENT, EFFECTIVE

Manufactured by: JOUAN CO LTD, 4F., No 10, Ln. 218, Sec. 2, Zhongxing Rd., Xindian Dist., New Taipei City, Taiwan (R.O.C), 23146

Product of Taiwan

Waived for general skincare product.

Shelf life: 5 years

This product is manufactured by Jouan Co., Ltd.
certified by the international GMP ISO22716